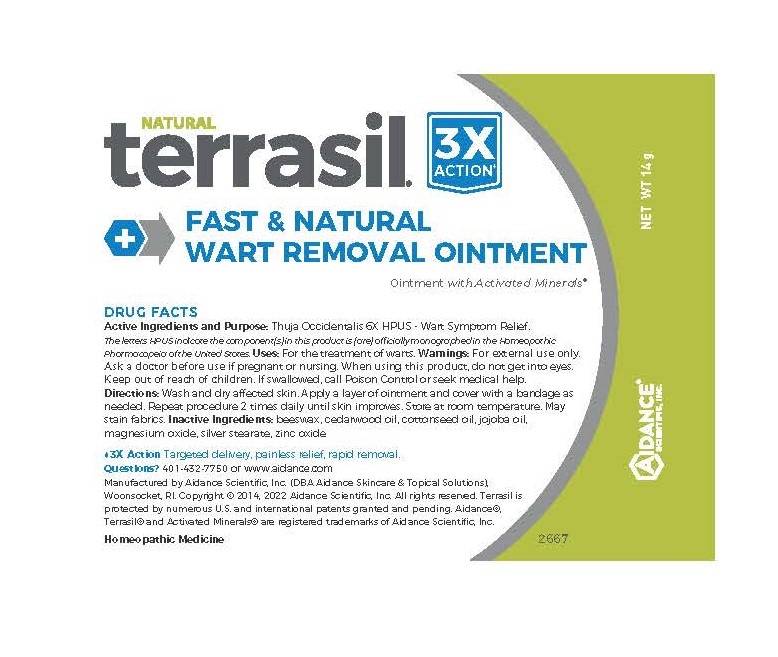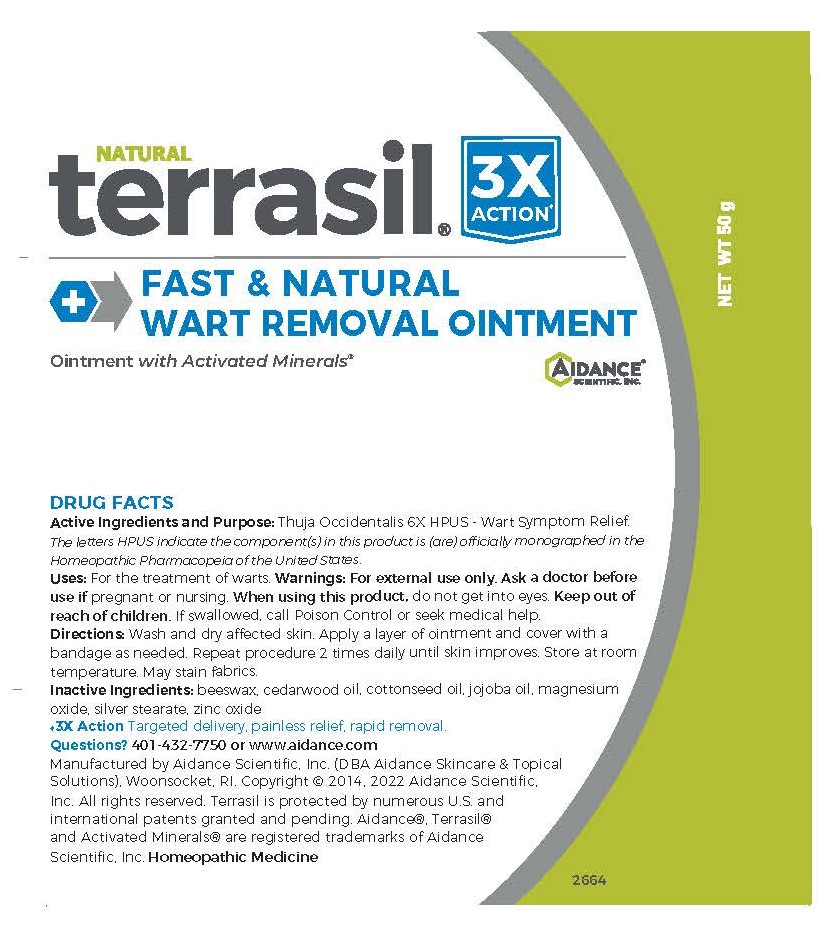 DRUG LABEL: Terrasil Fast and Natural Wart Removal
NDC: 24909-161 | Form: OINTMENT
Manufacturer: Aidance Skincare & Topical Solutions, LLC
Category: homeopathic | Type: HUMAN OTC DRUG LABEL
Date: 20250825

ACTIVE INGREDIENTS: THUJA OCCIDENTALIS LEAFY TWIG 6 [hp_X]/1 g
INACTIVE INGREDIENTS: JOJOBA OIL; JUNIPERUS VIRGINIANA OIL; MAGNESIUM OXIDE; SILVER STEARATE; YELLOW WAX; ZINC OXIDE; COCONUT OIL; COTTONSEED OIL; SUNFLOWER OIL

24909-161 terrasil Fast & Natural Wart Removal Ointment

Active Ingredient

Thuja 6X HPUS

The letters HPUS indicate the component(s) in this product is (are) officially monographed in the Homeopathic Pharmacopeia of the United States

Purpose

Wart Symptom Relief

Uses

For the treatment of warts.

Warnings

For external use only.
Ask a doctor before use if pregnant or nursing.
When using this product, do not get into eyes.

Keep out of reach of children. If swallowed, call poison control or seek medical help.

Directions

Wash and dry affected skin. Apply a layer of ointment and cover with a bandage as needed. Repeat procedure 2 times daily until skin improves. Store at room temperature. May stain fabrics.

Inactive Ingredients

beeswax, cedarwood oil, coconut oil*, cottonseed oil*, jojoba oil, magnesium oxide, silver stearate, sunflower oil*, zinc oxide.

*may contains this ingredients